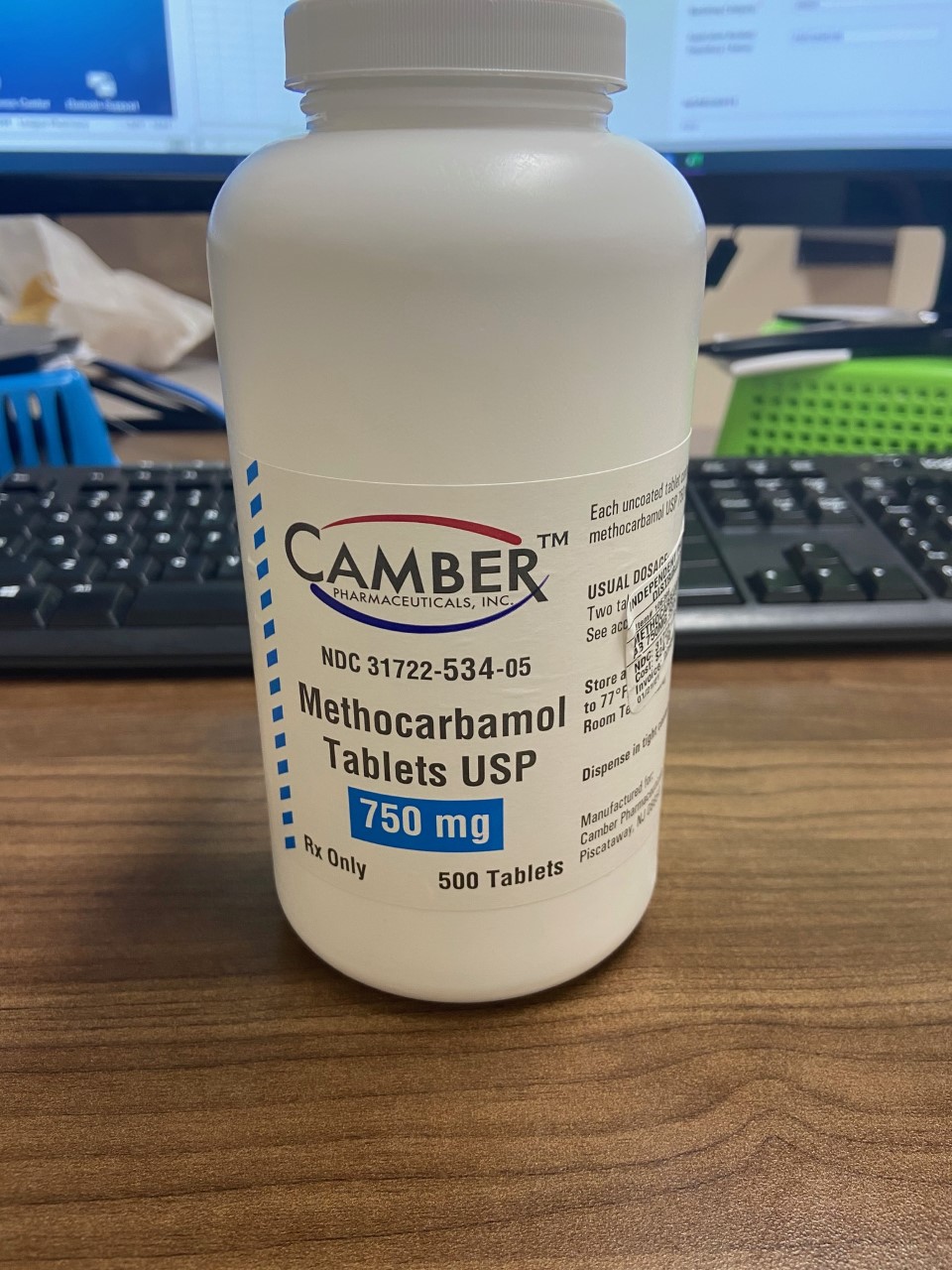 DRUG LABEL: METHOCARBAMOL
NDC: 80175-0534 | Form: TABLET
Manufacturer: Central Packaging
Category: prescription | Type: HUMAN PRESCRIPTION DRUG LABEL
Date: 20210226

ACTIVE INGREDIENTS: METHOCARBAMOL 750 mg/1 1

INDICATIONS AND USAGE

Methocarbamol tablets USP are indicated as an adjunct to rest, physical therapy, and other measures for the relief of discomfort associated with acute, painful musculoskeletal conditions. The mode of action of methocarbamol has not been clearly identified, but may be related to its sedative properties. Methocarbamol does not directly relax tense skeletal muscles in man.